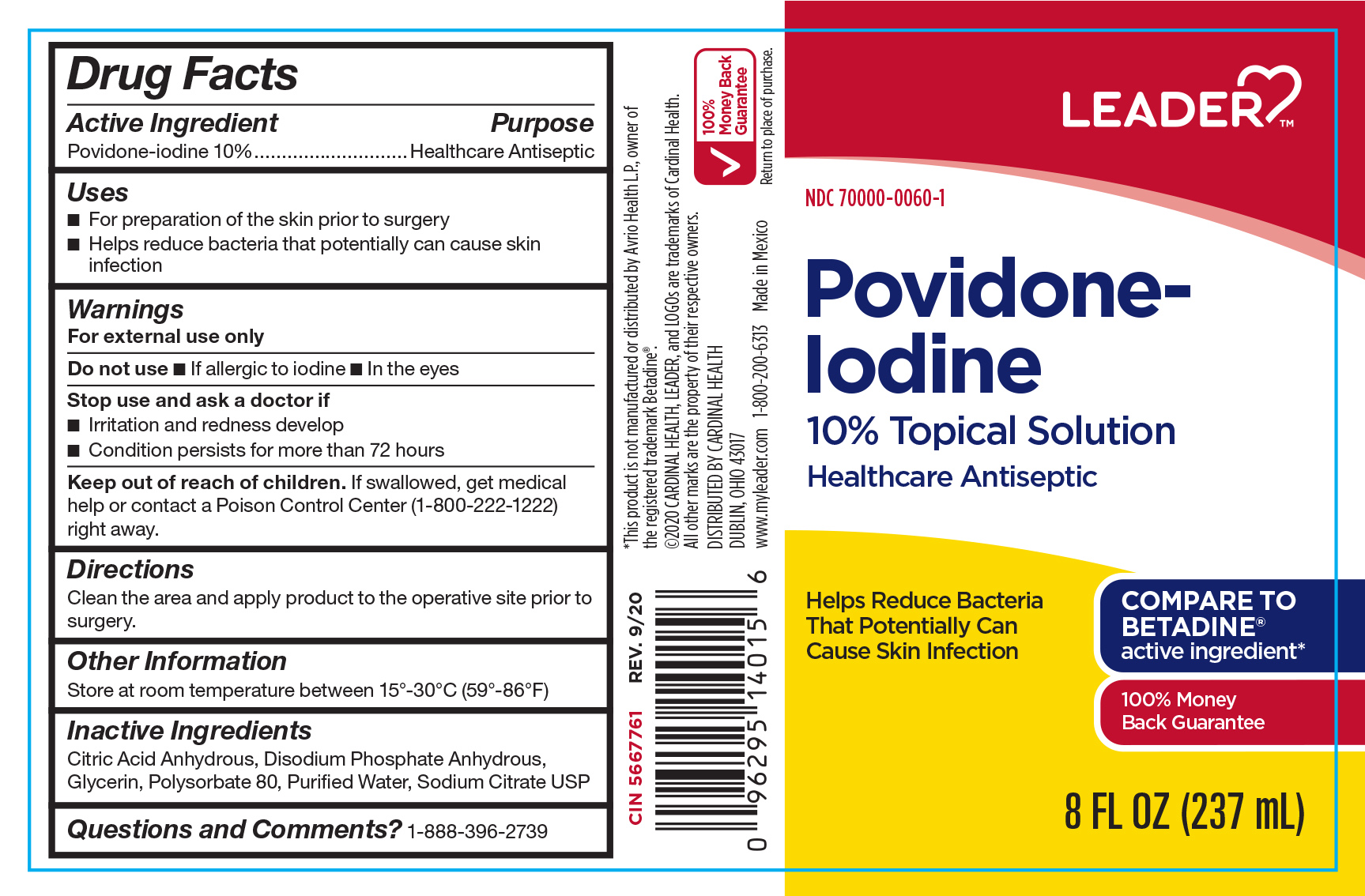 DRUG LABEL: Leader Povidone-Iodine 10% Topical Solution
NDC: 70000-0060 | Form: LIQUID
Manufacturer: Cardinal Health
Category: otc | Type: HUMAN OTC DRUG LABEL
Date: 20251125

ACTIVE INGREDIENTS: POVIDONE-IODINE 10 mg/1 mL
INACTIVE INGREDIENTS: GLYCERIN; WATER; POLYSORBATE 80; SODIUM CITRATE; ANHYDROUS CITRIC ACID; SODIUM PHOSPHATE, DIBASIC, ANHYDROUS

CR-5667761, NDC 70000-0060-1

Warnings

For external use only

Do Not Use

- if allergic to iodine
- in the eyes

Stop use and ask a doctor if

- irritation and redness develop
- condition persists for more than 72 hours

Keep out of reach of children. If swallowed, get medical help or contact a Poison Control Center (1-800-222-1222) right away.

Inactive Ingredients

Citric Acid Anhydrous, Disodium Phosphate Anhydrous, Glycerin, Polysorbate 80, Puried Water, Sodium Citrate USP

Active Ingredient

Povidone-iodine 10%

Purpose

Healthcare Antiseptic

Use

For preparation of the skin prior to surgery. Helps reduce bacteria that potentially can cause skin infection

Directions

Clean the area. Apply product to the operative site prior to surgery.

Other

Store at controlled room temperature 15º-30ºC (59º-86ºF).

Questions?

1-888-396-2739